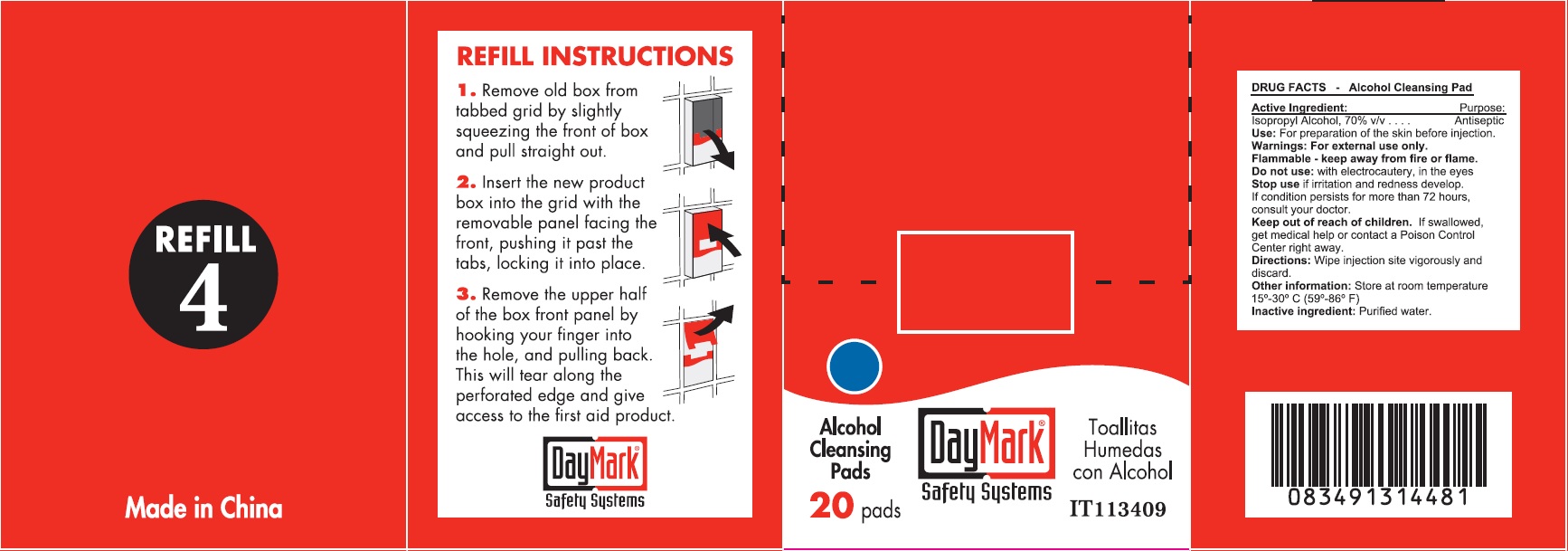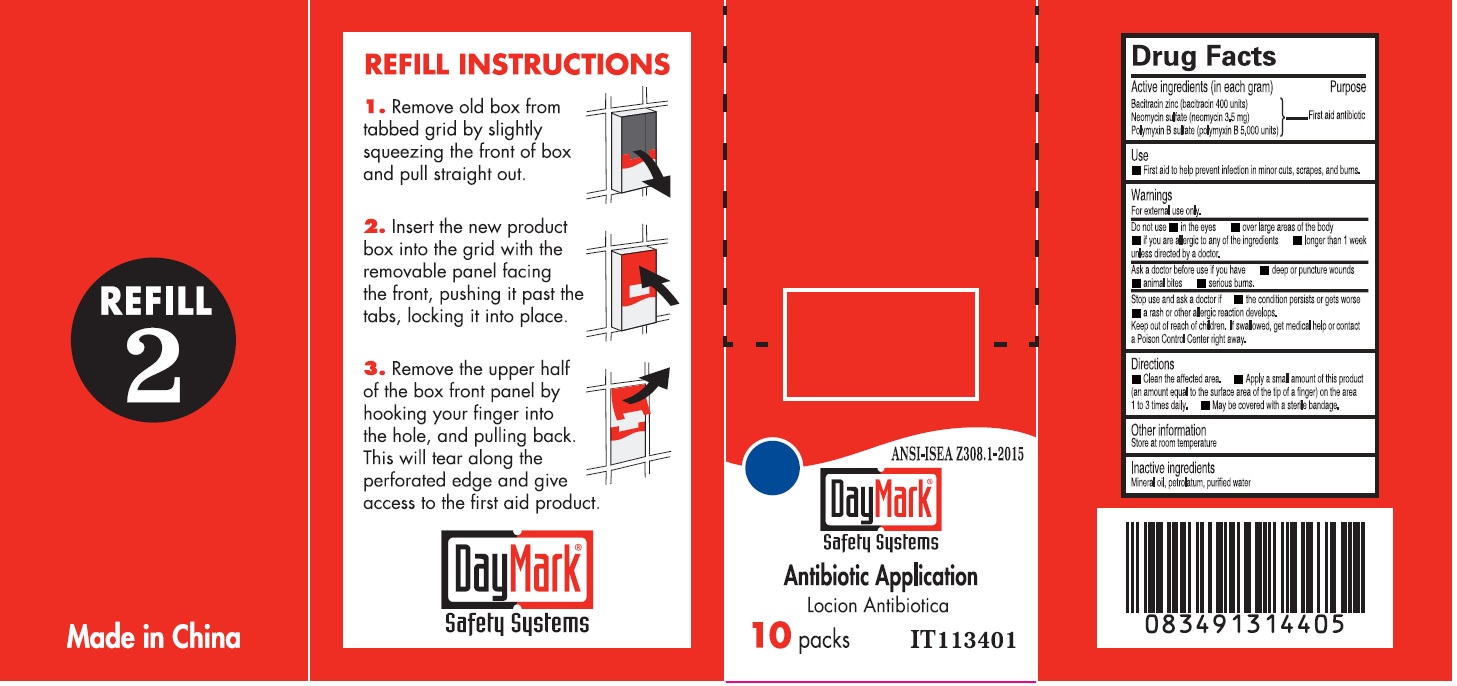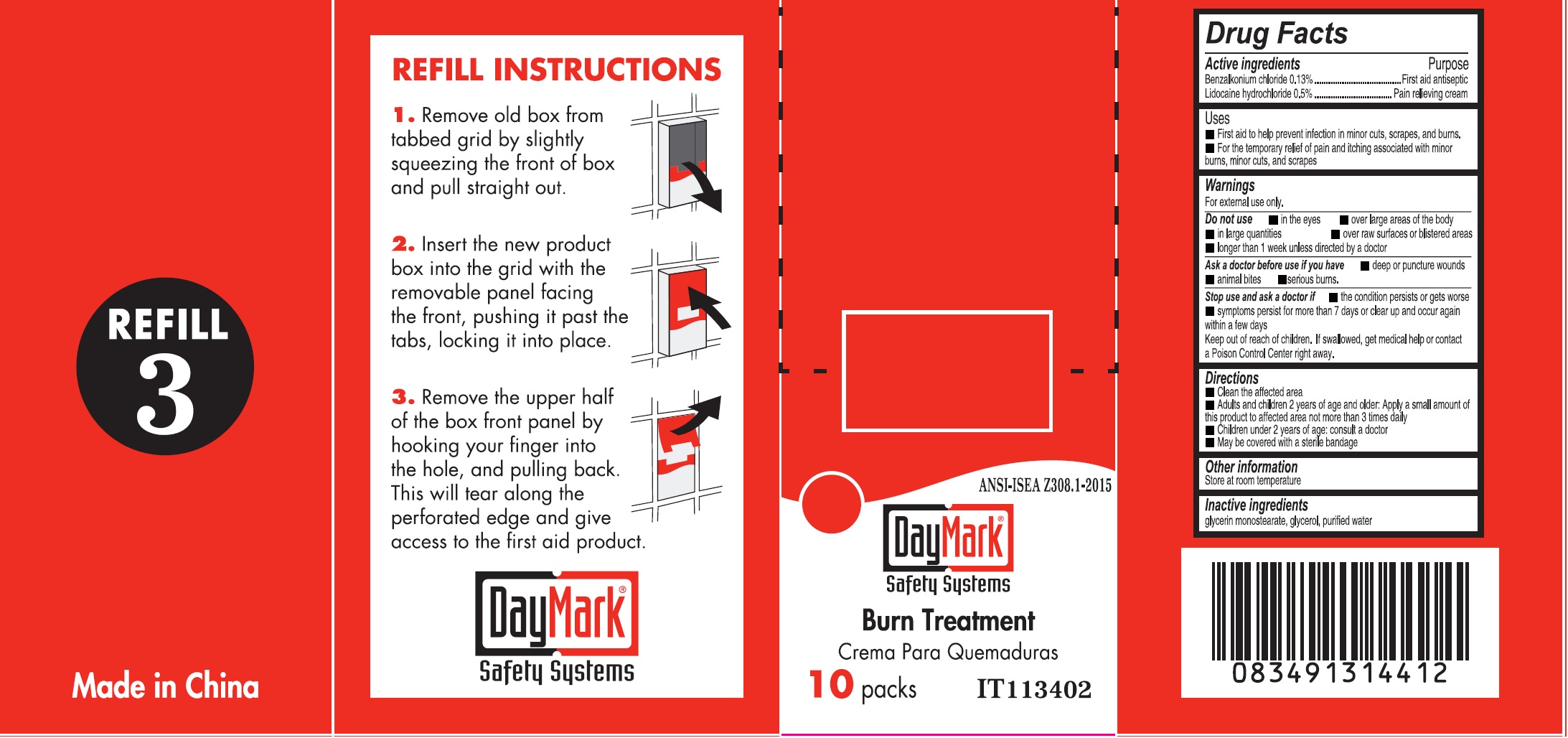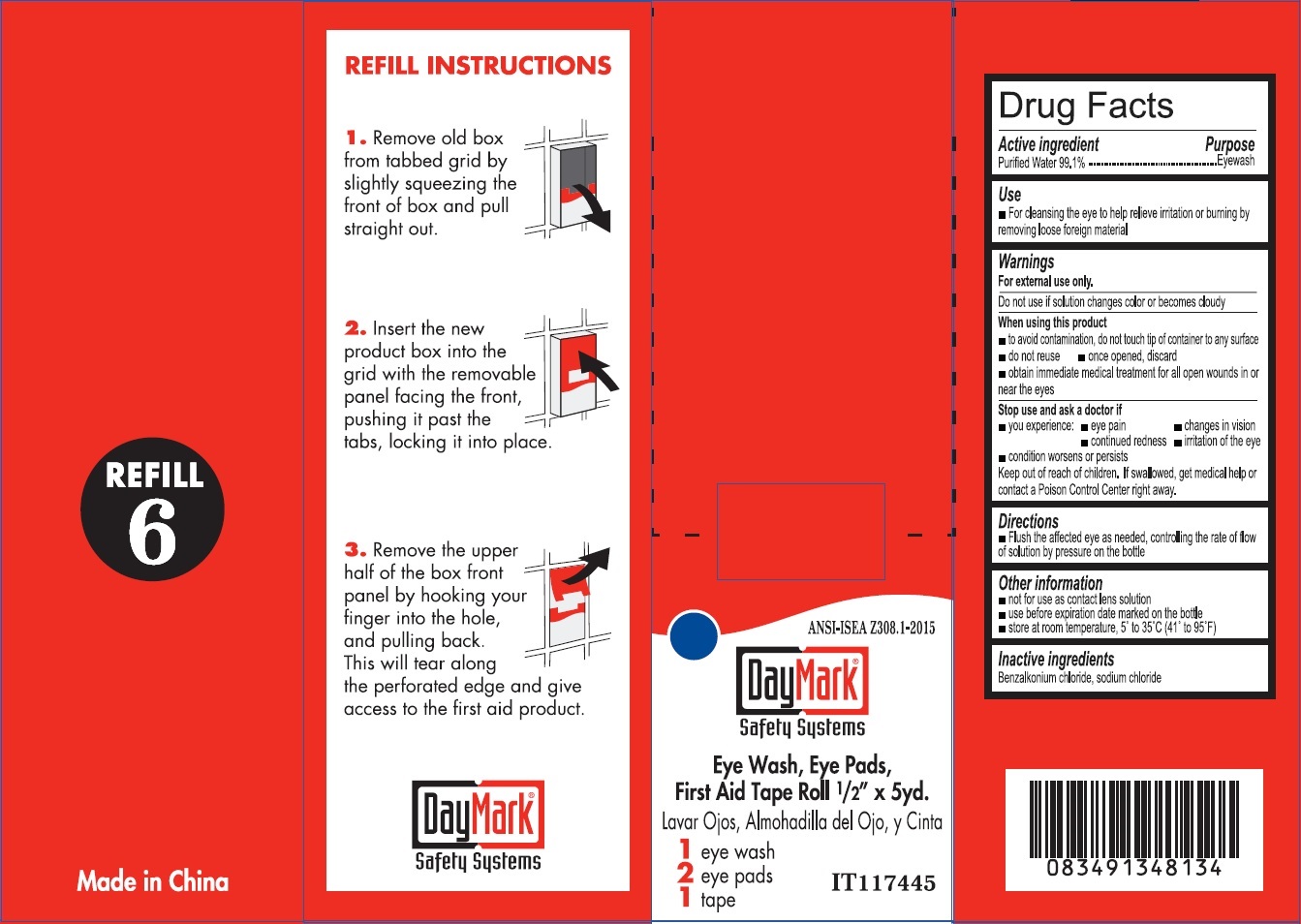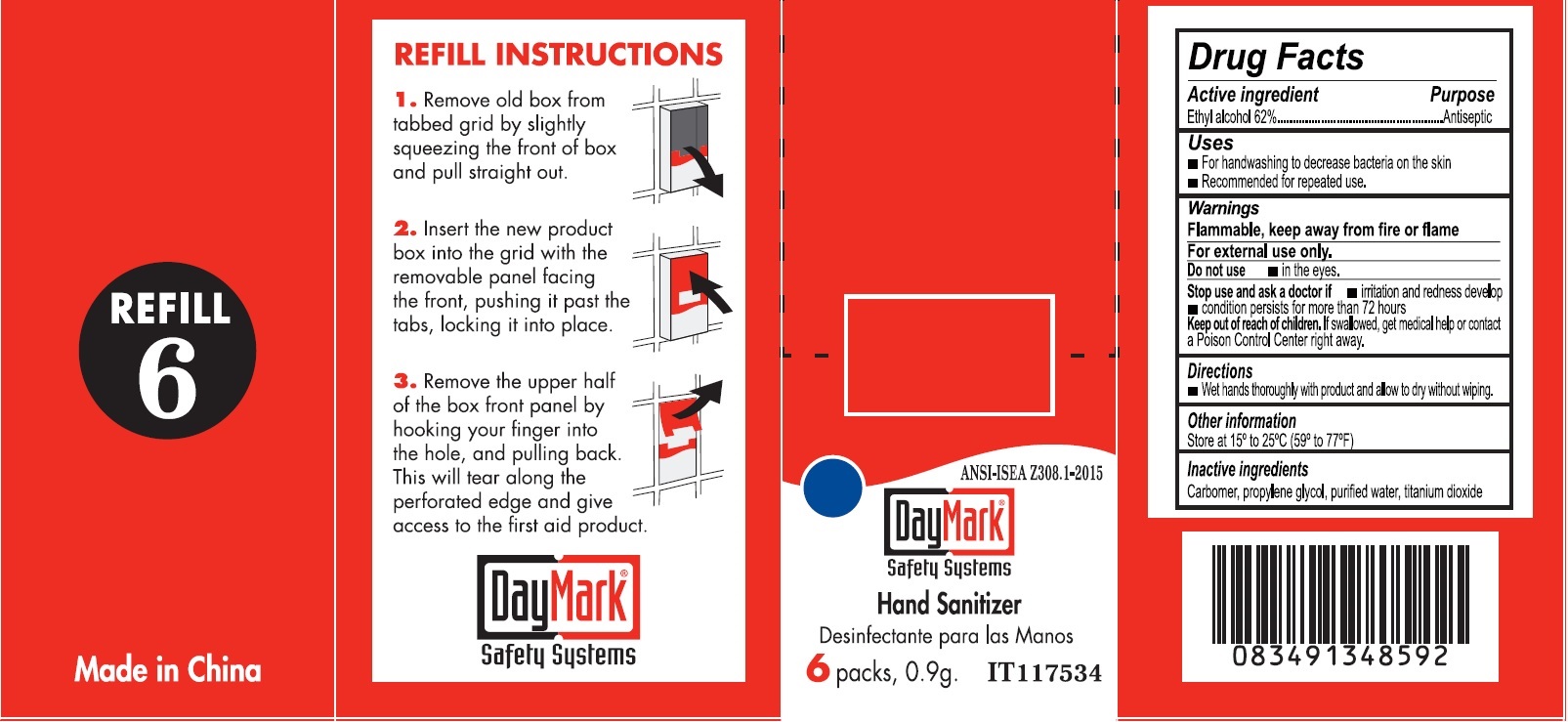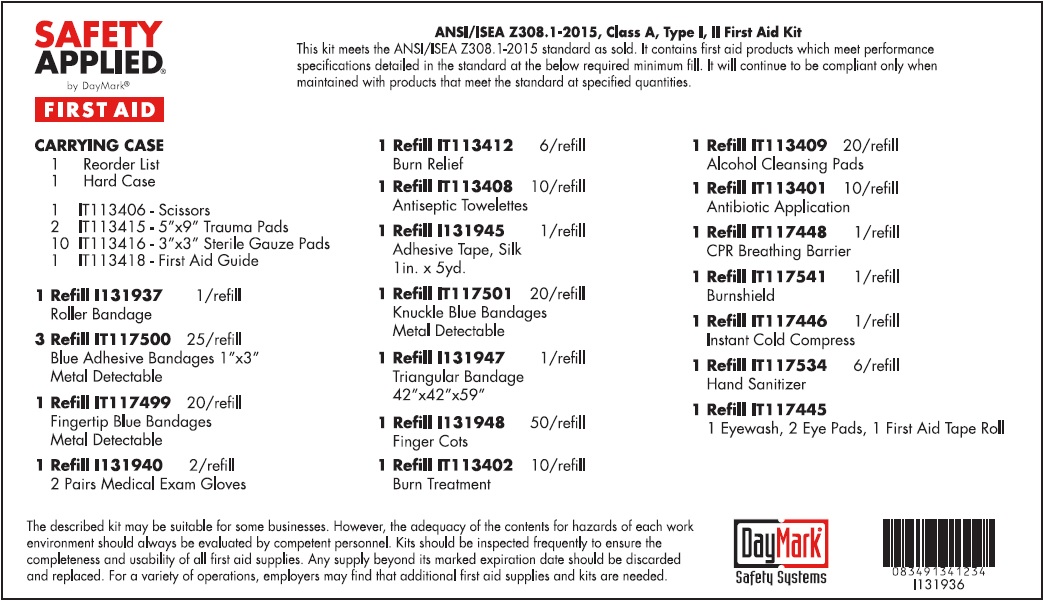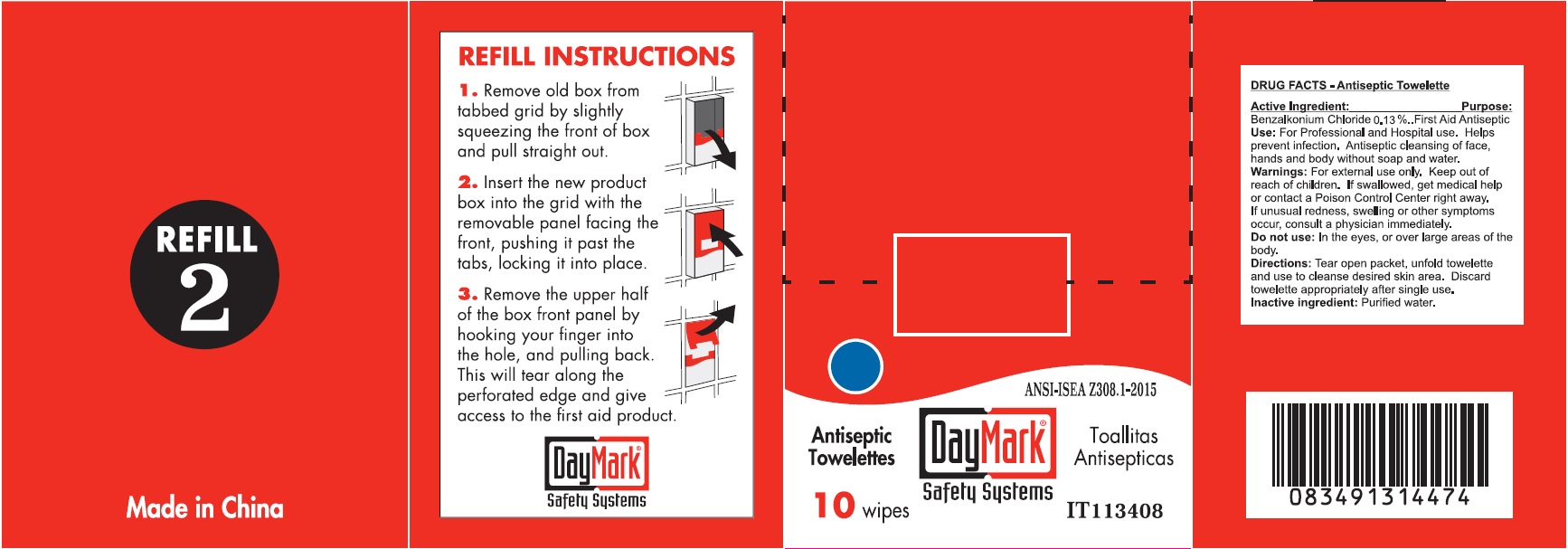 DRUG LABEL: Standard ANSI First Aid
NDC: 49687-0020 | Form: KIT | Route: OPHTHALMIC
Manufacturer: CMC Group, Inc.
Category: otc | Type: HUMAN OTC DRUG LABEL
Date: 20250402

ACTIVE INGREDIENTS: WATER 991 mg/1 mL; BENZALKONIUM CHLORIDE 0.13 g/100 g; ISOPROPYL ALCOHOL 70 g/100 g; BACITRACIN ZINC 400 [iU]/1 g; NEOMYCIN SULFATE 3.5 mg/1 g; POLYMYXIN B SULFATE 5000 [iU]/1 g; BENZALKONIUM CHLORIDE 0.13 g/100 g; LIDOCAINE HYDROCHLORIDE 0.5 g/100 g; ALCOHOL 0.62 g/1 g
INACTIVE INGREDIENTS: BENZALKONIUM CHLORIDE; SODIUM CHLORIDE; WATER; WATER; MINERAL OIL; PETROLATUM; WATER; GLYCERIN; WATER; CARBOXYPOLYMETHYLENE; PROPYLENE GLYCOL; WATER; TITANIUM DIOXIDE

Standard ANSI First Aid Kit

Active ingredient

Purified Water 99.1%

Purpose

Eyewash

Use

For cleansing the eye to help relieve irritation or burning by removing loose foreign material

Warnings

For external use only.

Do not use

if solution changes color or becomes cloudy

When using this product

• to avoid contamination, do not touch tip of container to any surface • do not reuse • once opened, discard • obtain immediate medical treatment for all open wounds in or near the eyes

Stop use and ask a doctor if

• you experience: • eye pain • changes in vision • continued redness • irritation of the eye • condition worsens or persists

Keep out of reach of children.

If swallowed, get medical help or contact a Poison Control Center right away.

Directions

• Flush the affected eye as needed, controlling the rate of flow of solution by pressure on the bottle

Other information

• not for use as contact lens solution

• use before expiration date marked on the bottle

• store at room temperature, 5° to 35°C (41° to 95°F)

Inactive ingredients

Benzalkonium chloride, sodium chloride

Active Ingredient:

Benzalkonium Chloride 0.13%

Purpose:

First Aid Antiseptic

Use:

For Professional and Hospital use. Helps prevent infection. Antiseptic cleansing of face, hands and body without soap and water.

Warnings:

For external use only.

Keep out of reach of children.

If swallowed, get medical help or contact a Poison Control Center right away. If unusual redness, swelling or other symptoms occur, consult a physician immediately.

Do not use:

In the eyes, or over large areas of the body.

Directions:

Tear open packet, unfold towelette and use to cleanse desired skin area. Discard towelette appropriately after single use.

Inactive ingredient:

Purified water.

Active Ingredient:

Isopropyl Alcohol, 70% v/v

Purpose:

Antiseptic

Use:

For preparation of the skin before injection.

Warnings:

For external use only. Flammable - keep away from fire or flame.

Do not use:

with electrocautery, in the eyes

Stop use

if irritation and redness develop. If condition persists for more than 72 hours, consult your doctor.

Keep out of reach of children.

If swallowed, get medical help or contact a Poison Control Center right away.

Directions:

Wipe injection site vigorously and discard.

Other information:

Store at room temperature 15°-30° C (59°-86° F)

Inactive ingredient:

Purified water.

Active ingredients (in each gram)

Bacitracin zinc (bacitracin 400 units) Neomycin sulfate (neomycin 3.5mg) Polymyxin B sulfate (polymyxin B 5,000 units)

Purpose

First aid antibiotic

Use

- First aid to help prevent infection in minor cuts, scrapes, and burns.

Warnings

For external use only

Do not use

• in the eyes • over large areas of the body • if you are allergic to any of the ingredient • longer than 1 week unless directed by a doctor.

Ask a doctor before use if you have

• deep or punture wounds • animal bites • serious burns.

Stop use and ask a doctor if

• the condition persists or gets worse • a rash or other allergic reaction develops.

Keep out of reach of children.

If swallowed, get medical help or contact a Poison Control Center right away.

Directions

• Clean the affected area. • Apply a small amount of this product (an amount equal to the surface area of the tip of a finger) on the area 1 to 3 times daily. • May be covered with a sterile bandage.

Inactive ingredients

Mineral oil, petrolatum, purified water

Active ingredients

Benzalkonium chloride 0.13% Lidocaine hydrochloride 0.5%

Purpose

First aid antiseptic

Pain relieving cream

Uses

- First aid to help prevent infection in minor cuts, scrapes, and burns.

- For the temporary relief of pain and itching associated with minor burns , minor cuts, and scrapes

Warnings

For external use only.

Do not use

• in the eyes • over large areas of the body • in large quantities • over raw surfaces or blistered areas • longer than 1 week unless directed by a doctor

Ask a doctor before use if you have

• deep or puncture wounds • animal bites • serious burns.

Stop use and ask a doctor if

• the condition persists or gets worse • symptoms persist for more than 7 days or clear up and occur again within a few days

Keep out of reah of children.

If swallowed, get medical help or contact a Poison Control Center right away.

Directions

- Clean the affected area

- Adults and children 2 years of age and older: Apply a small amount of this product to affected area not more than 3 times daily

- Children under 2 years of age: consult a doctor

- May be covered with a sterile bandage

Other information

Store at room temperature

Inactive ingredients

glycerin monostearate, glycerol, purified water

Active ingredient

Ethyl alcohol 62%

Purpose

Antiseptic

Uses

- For handwashing to decrease bacteria on the skin

- Recommended for repeated use.

Warnings

Flammable, keep away from fire or flame For external use only.

Do not use

- in the eyes.

Stop use and ask a doctor if

- irritation and redness develop

- condition persists for more than 72 hours

Keep out of reach children.

If swallowed, get medical help or contact a Poison Control Center right away.

Directions

- Wet hands thoroughly with product and allow to dry without wiping.

Other information

Store at 15° to 25°C (59° to 77°F)

Inactive ingredients

Carbomer, propylene glycol, purified water, titanium dioxide